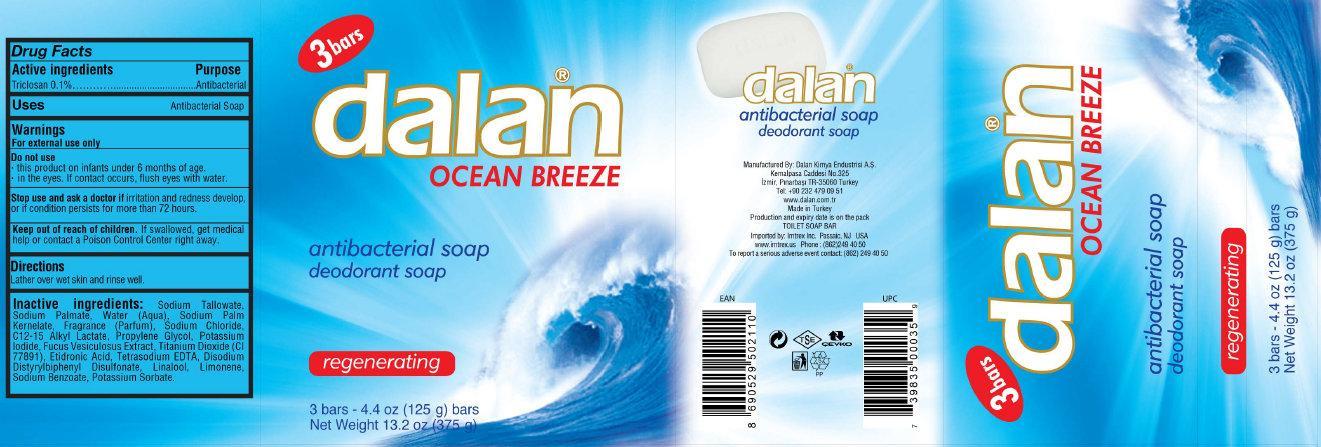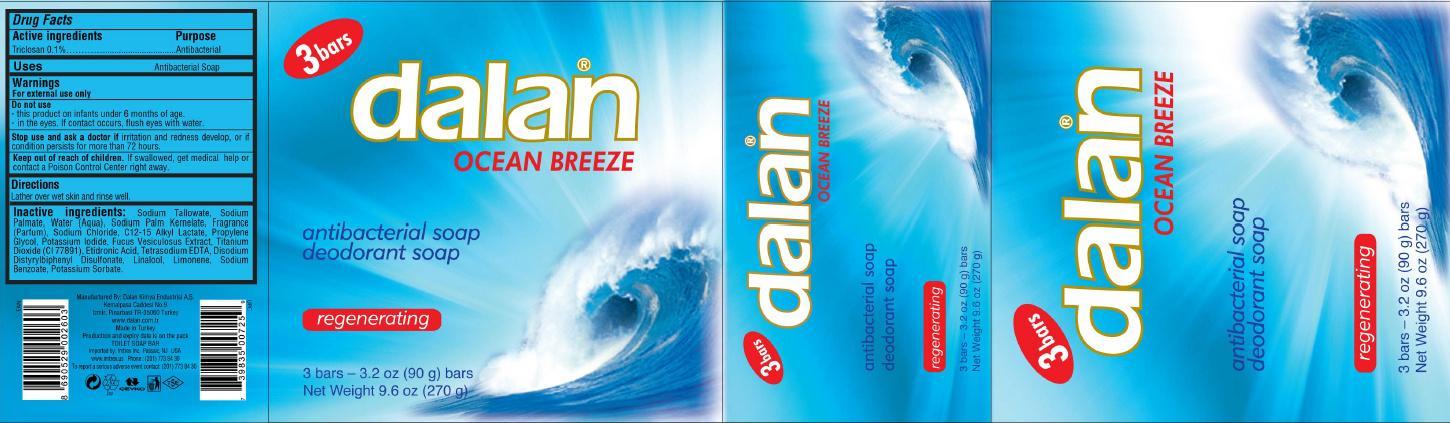 DRUG LABEL: dalan OCEAN BREEZE antibacterial deodorant
NDC: 51209-003 | Form: SOAP
Manufacturer: Dalan Kimya Endustri A.S.
Category: otc | Type: HUMAN OTC DRUG LABEL
Date: 20150202

ACTIVE INGREDIENTS: TRICLOSAN 0.1 g/100 g
INACTIVE INGREDIENTS: SODIUM TALLOWATE, BEEF; SODIUM PALMATE; WATER; SODIUM PALM KERNELATE; SODIUM CHLORIDE; PROPYLENE GLYCOL; POTASSIUM IODIDE; FUCUS VESICULOSUS; TITANIUM DIOXIDE; ETIDRONIC ACID; LINALOOL, (+)-; LIMONENE, (+)-; SODIUM BENZOATE; POTASSIUM SORBATE

dalan OCEAN BREEZE antibacterial soap deodorant soap

Active Ingredient / Purpose

PURPOSE

Triclosan 0.1% ...... Antibacterial

Uses

Antibacterial Soap

Warnings

For external use only
Do not use

- this product on infants under 6 months of age.
- in the eyes. If contact occurs, flush eyes with water.

Stop use and ask a doctor if irritation and redness develops or if condition persists for more than 72 hours.

Keep out of reach of children. If swallowed, get medical help or contact a Poison Control Center right away.

Directions

Lather over wet skin and rinse well

Inactive Ingredients:

Sodium Tallowate, Sodium Palmate, Water (Aqua), Sodium Palm Kernelate, Fragrance, Sodium Chloride, Alkyl Lactate, Propylene Glycol, Potassium Iodide, Fucus Vesiculosus Extract, Titanium Dioxide, Etidronic Acid, Linalool, Limonene, Sodium Benzoate, Potassium Sorbate.